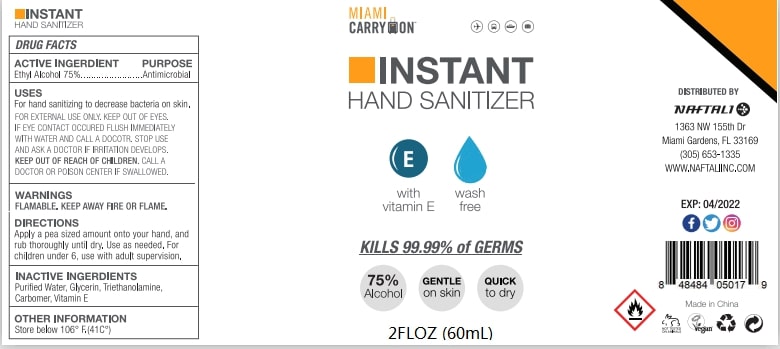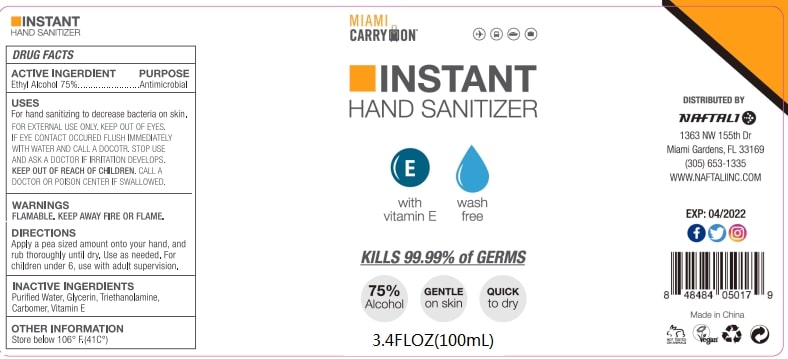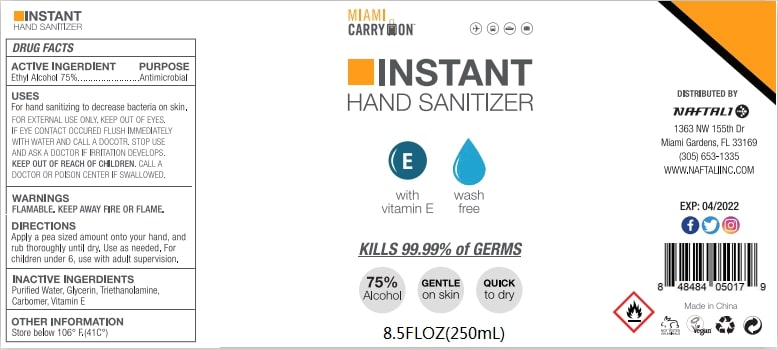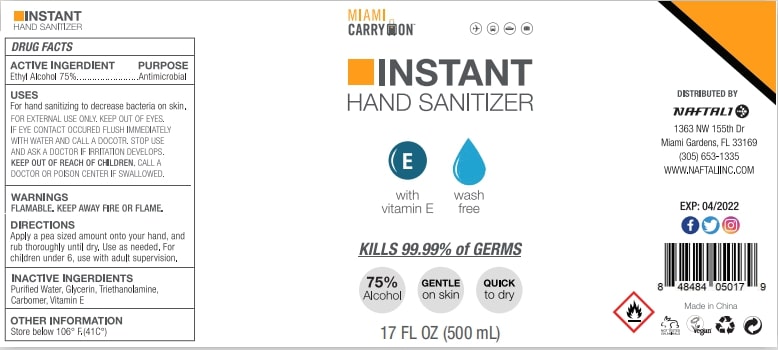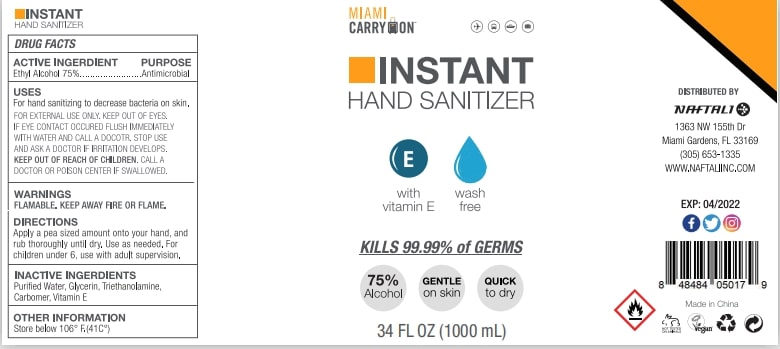 DRUG LABEL: HAND SANITIZER
NDC: 74763-012 | Form: GEL
Manufacturer: ZHEJIANG GAFLE AUTO CHEMICAL CO.,LTD
Category: otc | Type: HUMAN OTC DRUG LABEL
Date: 20220328

ACTIVE INGREDIENTS: ALCOHOL 75 mL/100 mL
INACTIVE INGREDIENTS: TROLAMINE; WATER; CARBOMER HOMOPOLYMER, UNSPECIFIED TYPE; GLYCERIN; .ALPHA.-TOCOPHEROL

HAND SANITIZER

ACTIVE INGERDIENT

Ethyl Alcohol 75%.

PURPOSE

Antimicrobial

USES

For hand sanitizing to decrease bacteria on skin,FOR EXTERNAL USE ONLY.KEEP OUT OF EYES.IF EYE CONTACT OCCLRED FLUSH IMMEDIATELY WITH WATER AND CALL A DOCOTR .STOP USE AND ASK A DOCTOR IF IRRITATION DEVELOPS.

WARNINGS

FLAMABLE.KEEP AWAY FIRE OR FLAME.

KEEP OUT OF REACH OF CHILDREN

CALL A DOCTOR OR POISON CENTER IF SWALLOWED.

DIRECTIONS

Apply a pea sized amount onto your hand, and rub thoroughly until dry,Use as needed,For children under 6,use with adult supervision.

OTHER INFORMATION

Store below 106°F.(41°C)

INACTIVE INGERDIENTS

Purified Water,Glycerin,Triethanolamine,Carbomer,Vitamin E.